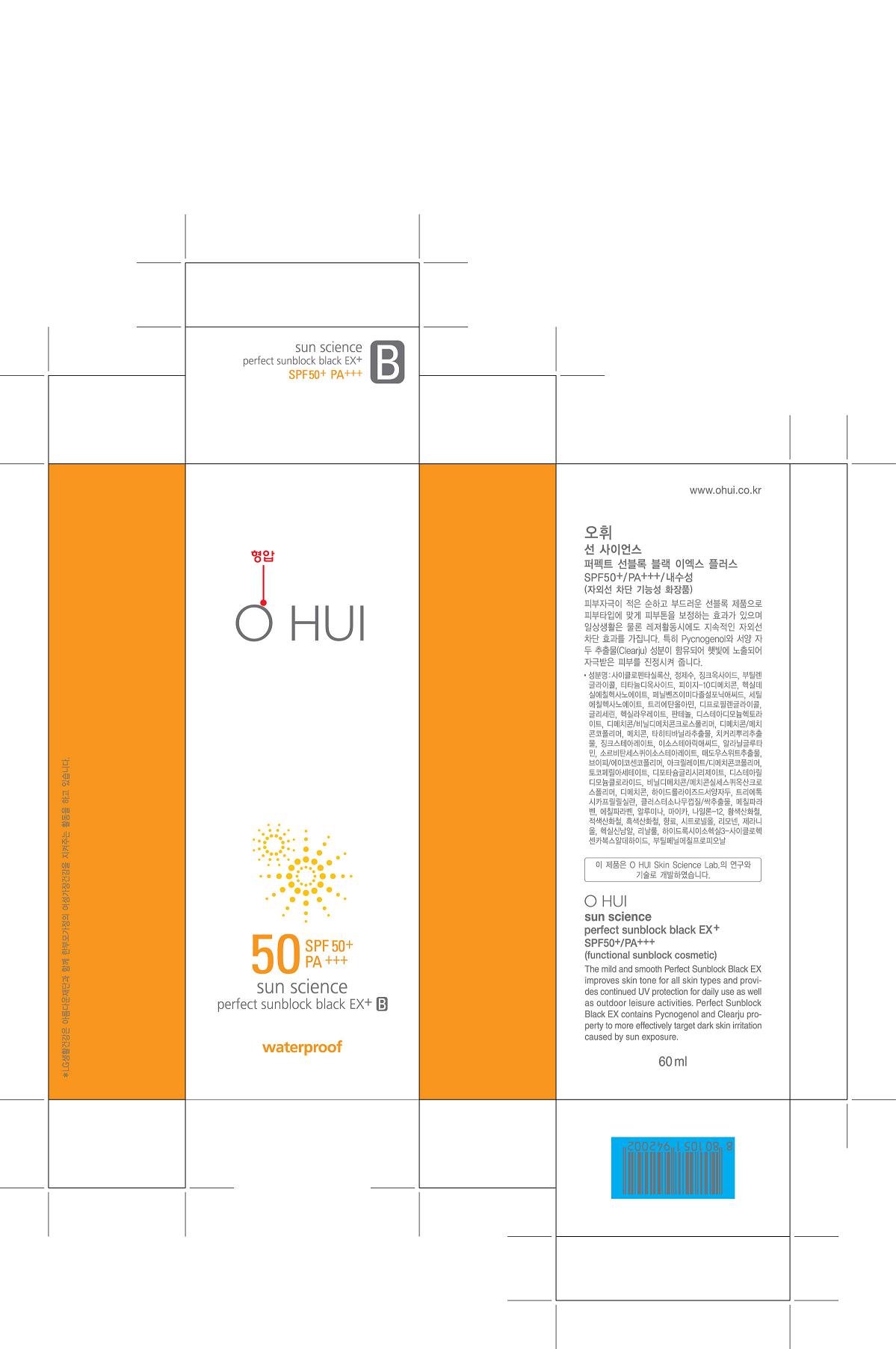 DRUG LABEL: OHUI SUN SCIENCE Perfect Sunblock black EX plus
NDC: 53208-538 | Form: CREAM
Manufacturer: LG Household and Healthcare, Inc.
Category: otc | Type: HUMAN OTC DRUG LABEL
Date: 20110803

ACTIVE INGREDIENTS: ZINC OXIDE 22.7 mL/100 mL; TITANIUM DIOXIDE 10 mL/100 mL; ENSULIZOLE 3.9 mL/100 mL
INACTIVE INGREDIENTS: WATER; BUTYLENE GLYCOL; CYCLOMETHICONE 5; CETYL ETHYLHEXANOATE; TROLAMINE; GLYCERIN; DIPROPYLENE GLYCOL; PANTHENOL; MAGNESIUM SULFATE, UNSPECIFIED; VANILLA; ISOSTEARIC ACID; ZINC STEARATE; METHYLPARABEN; GLYCYRRHIZINATE DIPOTASSIUM; ETHYLPARABEN; DISTEARYLDIMONIUM CHLORIDE

Drug Facts

ACTIVE INGREDIENT

ZINC OXIDE 22.7%

TITANIUM DIOXIDE 10%

ENSULIZOLE 3.9%

WARNINGS AND PRECAUTIONS

For external use only.

KEEP OUT OF REACH OF CHILDREN

If swallowed, get medical help or contact a Poison Control Center right away.

Stop use if a rash or irritation develops and lasts.

WHEN USING

Keep out of eyes. Rinse with water to remove.

PACKAGE LABEL

OHUI SUN SCIENCE Perfect Sunblock black EX plus